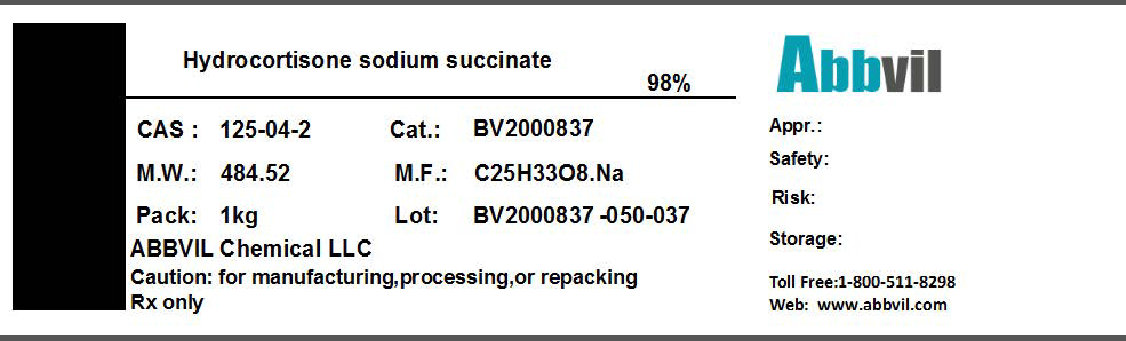 DRUG LABEL: HYDROCORTISONE SODIUM SUCCINATE
NDC: 86065-001 | Form: POWDER
Manufacturer: Abbvil Chemical LLC
Category: other | Type: BULK INGREDIENT
Date: 20160408

ACTIVE INGREDIENTS: HYDROCORTISONE SODIUM SUCCINATE 0.98 kg/1 kg

Hydrocortisone Sodium Succinate